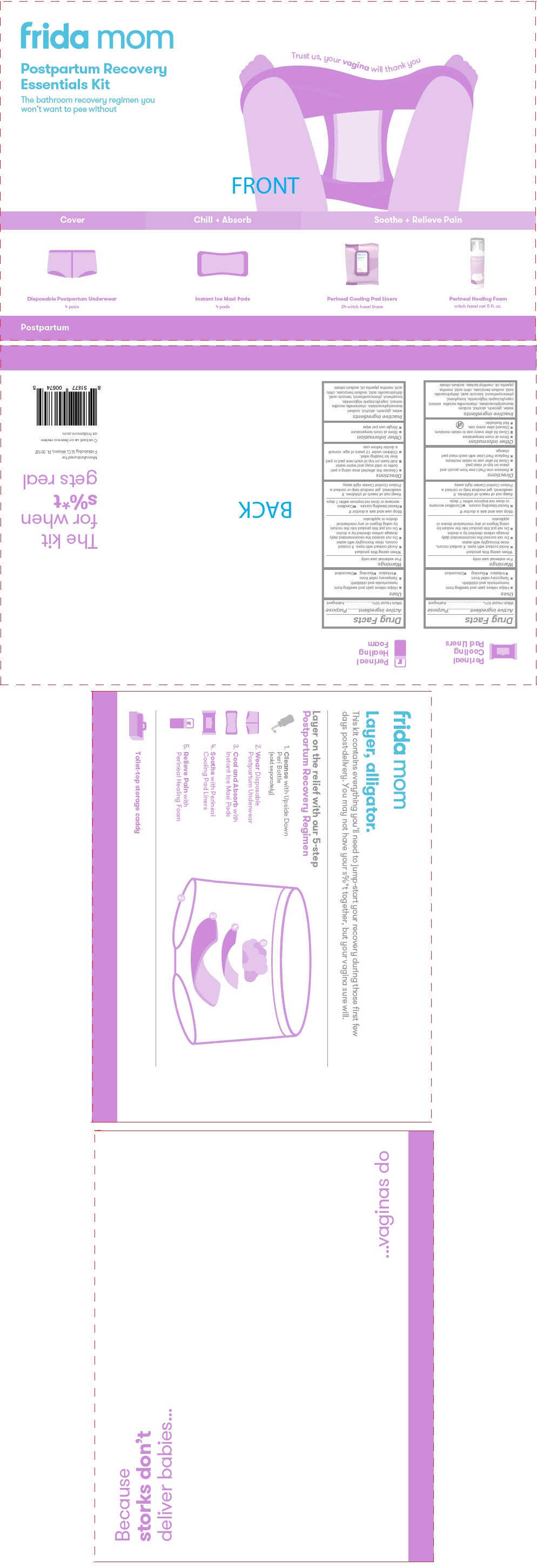 DRUG LABEL: frida mom Postpartum Recovery Essentials
NDC: 72705-200 | Form: KIT | Route: TOPICAL
Manufacturer: Fridababy, LLC
Category: otc | Type: HUMAN OTC DRUG LABEL
Date: 20241230

ACTIVE INGREDIENTS: WITCH HAZEL 0.5 g/1 1; WITCH HAZEL 0.5 g/1 g
INACTIVE INGREDIENTS: WATER; GLYCERIN; ALCOHOL; SODIUM LAUROAMPHOACETATE; MEDIUM-CHAIN TRIGLYCERIDES; TOCOPHEROL; PHENOXYETHANOL; BENZOIC ACID; DEHYDROACETIC ACID; SODIUM BENZOATE; CITRIC ACID MONOHYDRATE; PEPPERMINT OIL; MENTHYL LACTATE, (-)-; SODIUM CITRATE, UNSPECIFIED FORM; WATER; GLYCERIN; ALCOHOL; SODIUM LAUROAMPHOACETATE; MEDIUM-CHAIN TRIGLYCERIDES; TOCOPHEROL; PHENOXYETHANOL; BENZOIC ACID; DEHYDROACETIC ACID; SODIUM BENZOATE; CITRIC ACID MONOHYDRATE; PEPPERMINT OIL; SODIUM CITRATE, UNSPECIFIED FORM

frida mom Postpartum Recovery Essentials Kit

Perineal Cooling Pad Liners

Drug Facts

Active ingredient

Witch Hazel 50%

Purpose

Astringent

Uses

- Helps relieve pain and swelling from hemorrhoids and childbirth.
- Temporary relief from:
  - Irritation
  - Burning
  - Discomfort

Warnings

For external use only

When using this product

- Avoid contact with eyes. If contact occurs, rinse thoroughly with water.
- Do not exceed the recommended daily dosage unless directed by a doctor.
- Do not put this product into the rectum by using fingers or any mechanical device or applicator.

Stop use and ask a doctor if

- Rectal bleeding occurs.
- Condition worsens or does not improve within 7 days.

Keep out of reach of children.If swallowed, get medical help or contact a Poison Control Center right away.

Directions

- Remove one Pad Liner from pouch and place on top of maxi pad.
- Close lid after use to retain moisture.
- Replace Pad Liner with each maxi pad change.

Other information

- Store at room temperature
- Close lid after every use to retain moisture.
- Discard after every use.
- Not flushable.

Inactive ingredients

water, glycerin, alcohol, sodium lauroamphoacetate, chamomilla recutita extract, caprylic/capric triglyceride, tocopherol, phenoxyethanol, benzoic acid, dehydroacetic acid, sodium benzoate, citric acid, mentha piperita oil, menthyl lactate, sodium citrate

Perineal Healing Foam

Drug Facts

Active ingredient

Witch Hazel 50%

Purpose

Astringent

Uses

- Helps relieve pain and swelling from hemorrhoids and childbirth.
- Temporary relief from:
  - Irritation
  - Burning
  - Discomfort

Warnings

For external use only

When using this product

- Avoid contact with eyes. If contact occurs, rinse thoroughly with water.
- Do not exceed the recommended daily dosage unless directed by a doctor.
- Do not put this product into the rectum by using fingers or any mechanical device or applicator.

Stop use and ask a doctor if

- Rectal bleeding occurs.
- Condition worsens or does not improve within 7 days.

Keep out of reach of children.If swallowed, get medical help or contact a Poison Control Center right away.

Directions

- Cleanse the affected area using a peri bottle or mild soap and warm water.
- Add foam on top of each new pad or pad liner for healing relief.
- Children under 12 years of age: consult a doctor before use.

Other information

- Store at room temperature
- Single use per wipe

Inactive ingredients

water, glycerin, alcohol, sodium lauroamphoacetate, chamomilla recutita extract, caprylic/capric triglyceride, tocopherol, phenoxyethanol, benzoic acid, dehydroacetic acid, sodium benzoate, citric acid, mentha piperita oil, sodium citrate

PRINCIPAL DISPLAY PANEL - Kit Carton

fridamom

Postpartum Recovery
Essentials Kit

The bathroom recovery regimen you
won't want to pee without

Trust us, your vaginawill thank you

Cover

Disposable Postpartum Underwear
4 pairs

Chill + Absorb

Instant Ice Maxi Pads
4 pads

Soothe + Relieve Pain

Perineal Cooling Pad Liners
24 witch hazel liners

Perineal Healing Foam
witch hazel net 5 fl. oz.

Postpartum